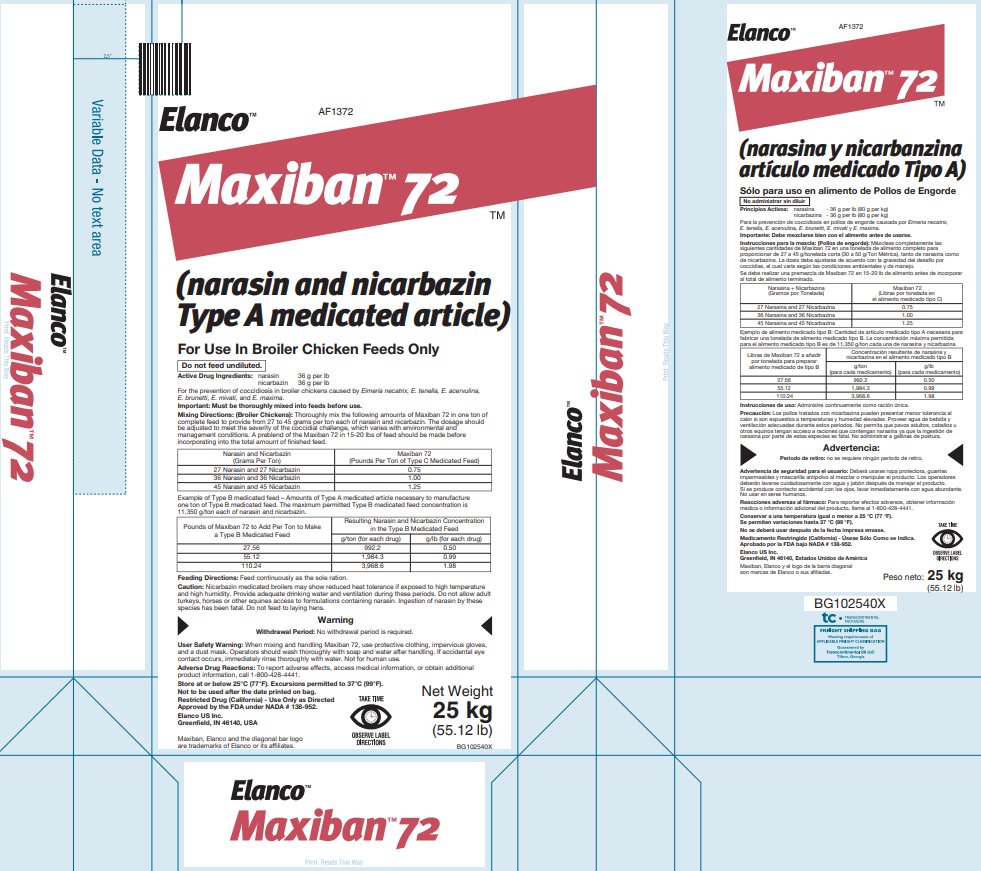 DRUG LABEL: Maxiban 72
NDC: 58198-1372 | Form: POWDER
Manufacturer: Elanco US Inc.
Category: animal | Type: OTC TYPE A MEDICATED ARTICLE ANIMAL DRUG LABEL
Date: 20240415

ACTIVE INGREDIENTS: narasin 36 g/0.45 kg; nicarbazin 36 g/0.45 kg

Elanco™

AF1372

Maxiban™ 72TM

(narasin and nicarbazin Type A medicated article)

For Use In Broiler Chicken Feeds Only

Do not feed undiluted.

Active Drug Ingredients:

narasin 36 g per lb

nicarbazin 36 g per lb

For the prevention of coccidiosis in broiler chickens caused by Eimeria necatrix, E. tenella, E. acervulina, E. brunetti, E. mivati, and E. maxima.

Important: Must be thoroughly mixed into feeds before use.

Mixing Directions: (Broiler Chickens):

Thoroughly mix the following amounts of Maxiban 72 in one ton of complete feed to provide from 27 to 45 grams per ton each of narasin and nicarbazin. The dosage should be adjusted to meet the severity of the coccidial challenge, which varies with environmental and management conditions. A preblend of the Maxiban 72 in 15-20 lbs of feed should be made before incorporating into the total amount of finished feed.

Narasin and Nicarbazin (Grams Per Ton) | Maxiban 72 (Pounds Per Ton of Type C Medicated Feed)
27 Narasin and 27 Nicarbazin | 0.75
36 Narasin and 36 Nicarbazin | 1.00
45 Narasin and 45 Nicarbazin | 1.25

Example of Type B medicated feed – Amounts of Type A medicated article necessary to manufacture one ton of Type B medicated feed. The maximum permitted Type B medicated feed concentration is 11,350 g/ton each of narasin and nicarbazin.

Pounds of Maxiban 72 to Add Per Ton to Make a Type B Medicated Feed | Resulting Narasin and Nicarbazin Concentration in the Type B Medicated Feed
Pounds of Maxiban 72 to Add Per Ton to Make a Type B Medicated Feed | g/ton (for each drug) | g/lb (for each drug)
27.56 | 992.2 | 0.50
55.12 | 1,984.3 | 0.99
110.24 | 3,968.6 | 1.98

Feeding Directions:

Feed continuously as the sole ration.

Caution:

Nicarbazin medicated broilers may show reduced heat tolerance if exposed to high temperature and high humidity. Provide adequate drinking water and ventilation during these periods. Do not allow adult turkeys, horses or other equines access to formulations containing narasin. Ingestion of narasin by these species has been fatal. Do not feed to laying hens.

Warning

Withdrawal Period: No withdrawal period is required.

User Safety Warning: When mixing and handling Maxiban 72, use protective clothing, impervious gloves, and a dust mask. Operators should wash thoroughly with soap and water after handling. If accidental eye contact occurs, immediately rinse thoroughly with water. Not for human use.

Adverse Drug Reactions:

To report adverse effects, access medical information, or obtain additional product information, call 1-800-428-4441.

STORAGE AND HANDLING

Store at or below 25°C (77°F). Excursions permitted to 37°C (99°F).

Not to be used after the date printed on bag.

Restricted Drug (California) - Use Only as Directed

Approved by the FDA under NADA # 138-952.

Elanco US Inc.

Greenfield, IN 46140, USA

Maxiban, Elanco and the diagonal bar logo are trademarks of Elanco or its affiliates.

TAKE TIME

OBSERVE LABEL DIRECTIONS

Net Weight 25 kg (55.12 lb)

BG102540X

Elanco™

AF1372

Maxiban™ 72TM

(narasina y nicarbanzina artículo medicado Tipo A)

Sólo para uso en alimento de Pollos de Engorde

BOXED WARNING

No administrar sin diluir

Principios Activos:

narasina - 36 g per lb (80 g per kg)

nicarbazina - 36 g per lb (80 g per kg)

Para la prevención de coccidiosis en pollos de engorde causada por Eimeria necatrix, E. tenella, E. acervulina, E. brunetti, E. mivati y E. maxima.

Importante: Debe mezclarse bien con el alimento antes de usarse.

Instrucciones para la mezcla: (Pollos de engorde):

Mézclese completamente las siguientes cantidades de Maxiban 72 en una tonelada de alimento completo para proporcionar de 27 a 45 g/tonelada corta (30 a 50 g/Ton Métrica), tanto de narasina como de nicarbazina. La dosis debe ajustarse de acuerdo con la gravedad del desafío por coccidias, el cual varía según las condiciones ambientales y de manejo.

Se debe realizar una premezcla de Maxiban 72 en 15-20 lb de alimento antes de incorporar al total de alimento terminado.

Narasina + Nicarbazina (Gramos por Tonelada) | Maxiban 72 (Libras por tonelada en el alimento medicado tipo C)
27 Narasina and 27 Nicarbazina | 0.75
36 Narasina and 36 Nicarbazina | 1.00
45 Narasina and 45 Nicarbazina | 1.25

Ejemplo de alimento medicado tipo B: Cantidad de artículo medicado tipo A necesaria para fabricar una tonelada de alimento medicado tipo B. La concentración máxima permitida para el alimento medicado tipo B es de 11,350 g/ton cada una de narasina y nicarbazina.

Libras de Maxiban 72 a añadir por tonelada para preparer alimento medicado de tipo B | Concentración resultante de narasina y nicarbazina en el alimento medicado tipo B
Libras de Maxiban 72 a añadir por tonelada para preparer alimento medicado de tipo B | g/ton (para cada medicamento) | g/lb (para cada medicamento)
27.56 | 992.2 | 0.50
55.12 | 1,984.3 | 0.99
110.24 | 3,968.6 | 1.98

Instrucciones de uso:

Administre continuamente como ración única.

Precaución:

Los pollos tratados con nicarbazina pueden presentar menor tolerancia al calor si son expuestos a temperaturas y humedad elevadas. Proveer agua de bebida y ventilación adecuadas durante estos períodos. No permita que pavos adultos, caballos u otros equinos tengan acceso a raciones que contengan narasina ya que la ingestión de narasina por parte de estas especies es fatal. No administrar a gallinas de postura.

Advertencia:

Período de retiro: no se requiere ningún período de retiro.

Advertencia de seguridad para el usuario: Deberá usarse ropa protectora, guantes impermeables y mascarilla antipolvo al mezclar o manipular el producto. Los operadores deberán lavarse cuidadosamente con agua y jabón después de manejar el producto. Si se produce contacto accidental con los ojos, lavar inmediatamente con agua abundante. No usar en seres humanos.

Reacciones adversas al fármaco:

Para reportar efectos adversos, obtener información medica o información adicional del producto, llame al 1-800-428-4441.

STORAGE AND HANDLING

Conservar a una temperatura igual o menor a 25 °C (77 °F).

Se permiten variaciones hasta 37 °C (99 °F).

No se deberá usar después de la fecha impresa envase.

Medicamento Restringido (California) - Úsese Sólo Como se Indica.

Aprobado por la FDA bajo NADA # 138-952.

Elanco US Inc.

Greenfield, IN 46140, Estados Unidos de América

Maxiban, Elanco y el logo de la barra diagonal son marcas de Elanco o sus afiliadas.

TAKE TIME

OBSERVE LABEL DIRECTIONS

Peso neto: 25 kg (55.12 lb)

BG102540X

Principal Display Panel – 25 kg Bag Label

Elanco™

AF1372

Maxiban™ 72TM

(narasin and nicarbazin Type A medicated article)

For Use In Broiler Chicken Feeds Only

Do not feed undiluted.